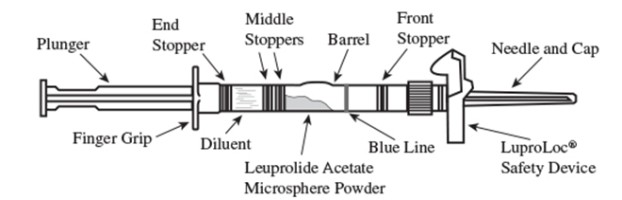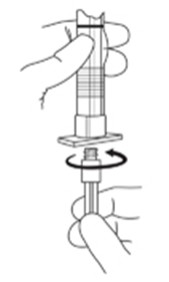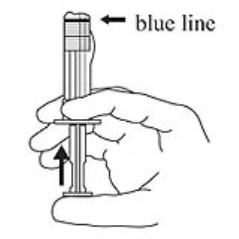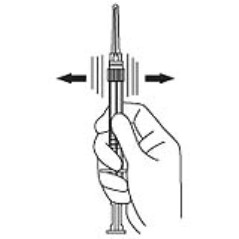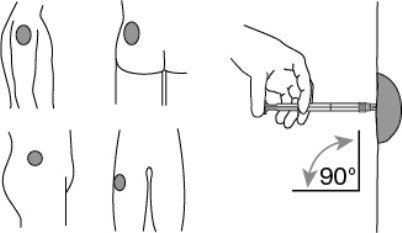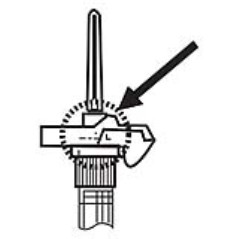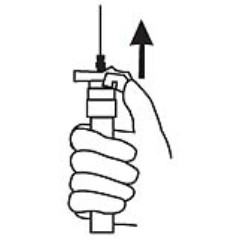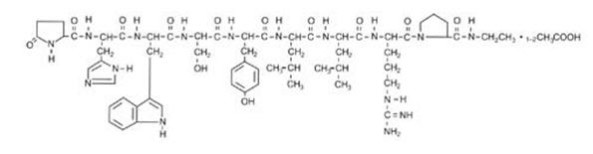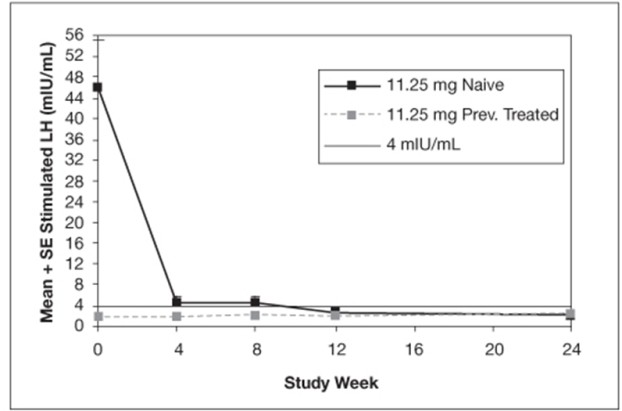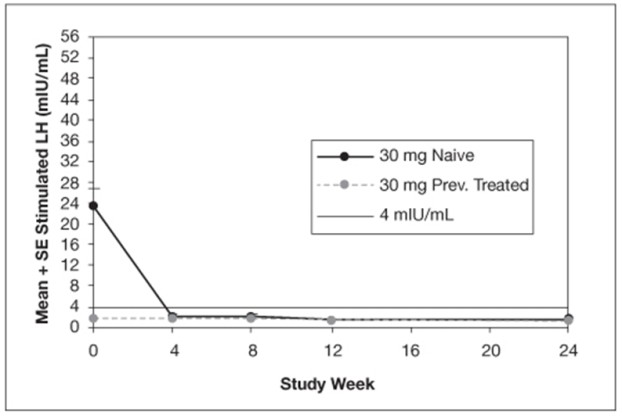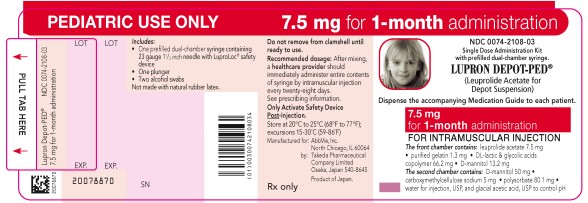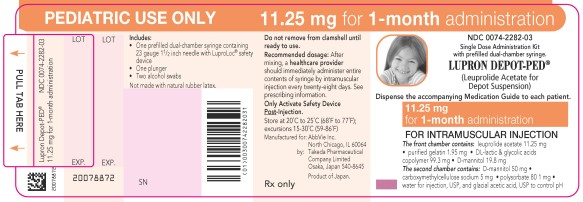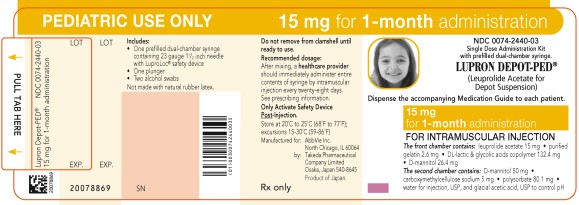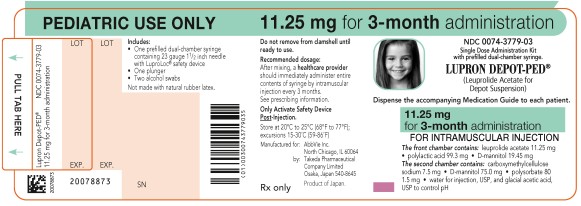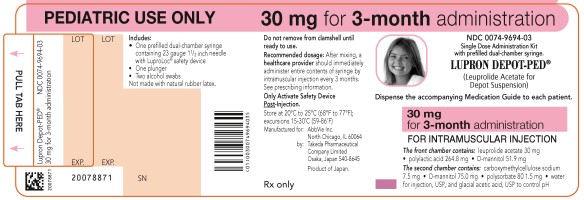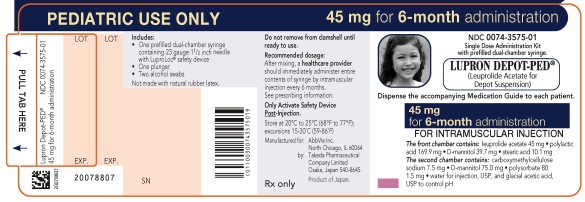 DRUG LABEL: Lupron Depot-PED
NDC: 0074-2108 | Form: KIT | Route: INTRAMUSCULAR
Manufacturer: AbbVie Inc.
Category: prescription | Type: HUMAN PRESCRIPTION DRUG LABEL
Date: 20251114

ACTIVE INGREDIENTS: LEUPROLIDE ACETATE 7.5 mg/1 mL
INACTIVE INGREDIENTS: ACETIC ACID; WATER; POLYSORBATE 80 1 mg/1 mL; MANNITOL 63.2 mg/1 mL; GELATIN, UNSPECIFIED 1.3 mg/1 mL; CARBOXYMETHYLCELLULOSE SODIUM, UNSPECIFIED FORM 5 mg/1 mL; ISOPROPYL ALCOHOL; WATER

HIGHLIGHTS OF PRESCRIBING INFORMATION

These highlights do not include all the information needed to use LUPRON DEPOT-PED safely and effectively. See full prescribing information for LUPRON DEPOT-PED.
LUPRON DEPOT-PED® (leuprolide acetate for depot suspension), for intramuscular use
Initial U.S. Approval: 1985

RECENT MAJOR CHANGES

Warnings and Precautions, Severe Cutaneous Adverse Reactions (5.4) 9/2025

1 INDICATIONS AND USAGE

LUPRON DEPOT-PED is a gonadotropin releasing hormone (GnRH) agonist indicated for the treatment of pediatric patients with central precocious puberty. (1)

2 DOSAGE AND ADMINISTRATION

- Must be administered by a healthcare professional. (2.1)
- Select appropriate LUPRON DEPOT-PED syringe for the intended dosing frequency and administer intramuscularly. (2.1)
- For 1-month administration: Starting dose is 7.5, 11.25, or 15 mg based on the patient’s weight. (2.2)
- For 3-month administration: Doses are either 11.25 or 30 mg. (2.3)
- For 6-month administration: Dose is 45 mg. (2.4)
- Monitor hormonal and clinical parameters during treatment to ensure adequate suppression. (2.2, 2.3, 2.4)
- Rotate injection site periodically. (2.5)
- See Full Prescribing Information for administration and reconstitution instructions. (2.5, 2.6)

3 DOSAGE FORMS AND STRENGTHS

For depot suspension: leuprolide acetate as a lyophilized powder supplied in single-dose, prefilled dual-chamber syringe with diluent (3):

- For 1-month administration: 7.5 mg, 11.25 mg, or 15 mg
- For 3-month administration: 11.25 mg or 30 mg
- For 6-month administration: 45 mg

4 CONTRAINDICATIONS

- Hypersensitivity reactions to GnRH, GnRH agonists or any of the excipients in LUPRON DEPOT-PED (4)
- Pregnancy (4, 8.1)

5 WARNINGS AND PRECAUTIONS

- Initial Rise of Gonadotropins and Sex Steroid Levels: During the early phase of therapy, gonadotropins and sex steroids may rise above baseline because of the initial stimulatory effect of the drug. Therefore, an increase in clinical signs and symptoms of puberty, including vaginal bleeding, may be observed during the first weeks of therapy or after subsequent doses. (5.1)
- Psychiatric events: Have been reported in patients taking GnRH agonists. Events include emotional lability, such as crying, irritability, impatience, anger, and aggression. Monitor for development or worsening of psychiatric symptoms. (5.2)
- Convulsions: Have been observed in patients with or without a history of seizures, epilepsy, cerebrovascular disorders, central nervous system anomalies or tumors, and in patients on concomitant medications that have been associated with convulsions. (5.3)
- Severe Cutaneous Adverse Reactions (SCARs): Have been reported in patients receiving GnRH agonists, including leuprolide products. Interrupt LUPRON DEPOT-PED if signs or symptoms of SCARs develop. Permanently discontinue LUPRON DEPOT-PED if a SCAR is confirmed. (5.4)
- Pseudotumor Cerebri (Idiopathic Intracranial Hypertension): Have been reported in pediatric patients receiving GnRH agonists, including LUPRON DEPOT-PED. Monitor patients for headache, papilledema, and blurred vision. (5.5)

6 ADVERSE REACTIONS

- Adverse events related to suppression of endogenous sex steroid secretion and injection site reactions including abscess may occur with LUPRON DEPOT-PED 7.5 mg, 11.25 mg, or 15 mg for 1-month administration. (6.1, 6.2)
- In the clinical studies for LUPRON DEPOT-PED 7.5 mg, 11.25 mg, or 15mg for 1-month administration the most common (≥2%) adverse reactions were: emotional lability, headache, general pain, acne/seborrhea, rash including erythema multiforme and vaginitis/vaginal bleeding/vaginal discharge. (6.1)
- In the clinical studies for LUPRON DEPOT-PED 11.25 mg or 30 mg for 3-month administration the most common (>2%) adverse reactions were: injection site pain, weight increased, headache, mood altered, and injection site swelling. (6.1)
- In the clinical study for LUPRON DEPOT-PED 45 mg for 6-month administration the most common (≥4%) adverse reactions were: injection site reactions, headache, psychiatric events, abdominal pain, diarrhea, hemorrhage, nausea and vomiting, pyrexia, pruritus, pain in extremity, rash, back pain, ligament sprain, weight increased, fracture, breast tenderness, insomnia, chest pain, and hyperhidrosis. (6.1)

To report SUSPECTED ADVERSE REACTIONS, contact AbbVie Inc. at 1-800-633-9110 or FDA at 1-800-FDA-1088 or www.fda.gov/medwatch

FULL PRESCRIBING INFORMATION

1 INDICATIONS AND USAGE

LUPRON DEPOT-PED is indicated for the treatment of pediatric patients with central precocious puberty (CPP).

2 DOSAGE AND ADMINISTRATION

2.1 Important Dosing Information

- LUPRON DEPOT-PED must be administered by a healthcare professional.
- Individualize the dose of LUPRON DEPOT-PED for each patient.
- Select the appropriate LUPRON-DEPOT PED syringe for the intended dosing frequency and administer intramuscularly.
- Each LUPRON DEPOT-PED strength and formulation has different release characteristics. Do not use partial syringes or a combination of syringes to achieve a particular dose.
- In the case of inadequate suppression of pituitary gonadotropins and peripheral sex steroids with a maximal dosage, consider other available gonadotropin releasing hormone (GnRH) agonists indicated for the treatment of central precocious puberty.
- Discontinue LUPRON DEPOT-PED at the appropriate age of onset of puberty.

2.2 Dosage and Recommended Monitoring for 1-Month Administration

- Administer LUPRON DEPOT-PED 7.5 mg, 11.25 mg, or 15 mg for 1-month administration as a single-dose intramuscular injection once every month.
- The starting dose is based on the patient's weight (see Table 1).

Table 1. Dosage Recommendations Based on Body Weight for LUPRON DEPOT-PED for 1-Month Administration
Body Weight | Once Monthly Recommended Dosage
Less than or equal to 25 kg | 7.5 mg
Greater than 25 kg up to 37.5 kg | 11.25 mg
Greater than 37.5 kg | 15 mg

- The dosage may need to be adjusted with changes in body weight.
- If adequate hormonal and clinical suppression is not achieved with the starting dose, increase the dosage to the next available higher dose (e.g., 11.25 mg or 15 mg at the next monthly injection).
- Monitor response with a GnRH stimulation test, basal luteinizing hormone (LH) or serum concentration of sex steroid levels beginning 1 to 2 months following initiation of therapy, with changing doses, or further as judged clinically appropriate in order to confirm maintenance of efficacy.
- Assess height (for calculation of growth rate) and bone age every 6 to 12 months.

2.3 Dosage and Recommended Monitoring for 3-Month Administration

- Use LUPRON DEPOT-PED 11.25 mg or 30 mg for 3-month administration once every three months (12 weeks) as a single-dose intramuscular injection.
- Monitor response with a GnRH stimulation test, basal LH or serum concentration of sex steroid levels at months 2 to 3, month 6 and further as judged clinically appropriate, to confirm maintenance of efficacy.
- Assess height (for calculation of growth rate) and bone age every 6 to 12 months.

2.4 Dosage and Recommended Monitoring for 6-Month Administration

- Use LUPRON DEPOT-PED 45 mg for 6-month administration once every six months (24 weeks) as a single-dose intramuscular injection.
- Monitor response with a GnRH stimulation test, basal LH or serum concentration of sex steroid levels at months 5 to 6 and further as judged clinically appropriate, to confirm maintenance of efficacy.
- Assess height (for calculation of growth rate) and bone age every 6 to 12 months.

2.5 Important Administration Instructions

- Administer LUPRON DEPOT-PED as a single-dose intramuscular injection into the gluteal area, anterior thigh, or shoulder.
- Rotate injection sites within the same region from one injection to the next.
- Inject immediately after reconstitution. Discard if not used within 2 hours.

2.6 Reconstitution Instructions

1. Visually inspect the LUPRON DEPOT-PED powder and diluent. Do not use the syringe if clumping or caking is evident. A thin layer of powder on the wall of the syringe is considered normal prior to mixing with the diluent. The diluent should appear clear and free from particulate matter. Do not use the diluent if it is not clear or there is particulate matter.

2. To prepare for injection, screw the white plunger into the end stopper until the stopper begins to turn. (see Figure 1 and Figure 2)

Figure 1

LuproLoc Safety Device should be activated after product injection, refer to Step 9 (Figure 7).

Figure 2

3. Hold the syringe upright. Release the diluent by slowly pushing the plunger for 6 to 8 seconds until the first stopper is at the blue line in the middle of the barrel. (Figure 3)

Figure 3

4. Keep the syringe upright. Mix the powder thoroughly by gently shaking the syringe until the powder forms a uniform suspension. The suspension will appear milky. If the powder adheres to the stopper or caking/clumping is present, tap the syringe with your finger to disperse. Do not use if any of the powder has not gone into suspension. (Figure 4)

Figure 4

5. Hold the syringe upright. With the opposite hand pull the needle cap upward without twisting.

6. Keep the syringe upright. Advance the plunger to expel the air from the syringe.
Now the syringe is ready for injection.

7. After cleaning the injection site with an alcohol swab, administer the intramuscular injection by inserting the needle at a 90 degree angle into the deltoid, gluteal area, or anterior thigh. (Figure 5)

Figure 5

NOTE: Aspirated blood would be visible just below the luer lock connection if a blood vessel is accidentally penetrated. If present, blood can be seen through the transparent LuproLoc® safety device. If blood is present remove the needle immediately. Do not inject the medication. (Figure 6)

Figure 6

8. Inject the entire contents of the syringe intramuscularly immediately after reconstitution. The suspension settles very quickly following reconstitution.

9. Withdraw the needle. Once the syringe has been withdrawn, activate immediately the LuproLoc® safety device by pushing the arrow on the lock upward towards the needle tip with the thumb or finger, as illustrated, until the needle cover of the safety device is fully extended over the needle and a click is heard or felt. (Figure 7)

Figure 7

3 DOSAGE FORMS AND STRENGTHS

For depot suspension: a white lyophilized powder supplied in a single-dose, prefilled dual-chamber syringe with a colorless diluent is available as:

- For 1-month administration: 7.5 mg, 11.25 mg, or 15 mg of leuprolide acetate
- For 3-month administration: 11.25 mg or 30 mg of leuprolide acetate
- For 6-month administration: 45 mg of leuprolide acetate

4 CONTRAINDICATIONS

- Hypersensitivity to GnRH, GnRH agonists or any of the excipients in LUPRON DEPOT-PED. Anaphylactic reactions to synthetic GnRH or GnRH agonists have been reported [see Adverse Reactions (6.2)].
- Pregnancy: LUPRON DEPOT-PED may cause fetal harm [see Use in Specific Populations (8.1)].

5 WARNINGS AND PRECAUTIONS

5.1 Initial Rise of Gonadotropins and Sex Steroid Levels

During the early phase of therapy or after subsequent doses, gonadotropins and sex steroids may rise above baseline because of a transient stimulatory effect of the drug [see Clinical Pharmacology (12.2)]. Therefore, an increase in clinical signs and symptoms of puberty, including vaginal bleeding, may be observed during the first weeks of therapy or after subsequent doses [see Adverse Reactions (6)].

5.2 Psychiatric Events

Psychiatric events have been reported in patients taking GnRH agonists, including LUPRON DEPOT-PED. Postmarking reports with this class of drugs include symptoms of emotional lability, such as crying, irritability, impatience, anger and aggression. Monitor for development or worsening of psychiatric symptoms during treatment with LUPRON DEPOT-PED [see Adverse Reactions (6.2)].

5.3 Convulsions

Postmarketing reports of convulsions have been observed in patients receiving GnRH agonists, including LUPRON DEPOT-PED. These included patients with a history of seizures, epilepsy, cerebrovascular disorders, central nervous system anomalies or tumors, and patients on concomitant medications that have been associated with convulsions such as bupropion and SSRIs. Convulsions have also been reported in patients in the absence of any of the conditions mentioned above [see Adverse Reactions (6.2)].

5.4 Severe Cutaneous Adverse Reactions

Severe cutaneous adverse reactions (SCARs) have been reported in patients receiving GnRH agonists, including leuprolide products [see Adverse Reactions (6.2)]. These reactions include Stevens-Johnson syndrome/toxic epidermal necrolysis (SJS/TEN), drug reaction with eosinophilia and systemic symptoms (DRESS), and acute generalized exanthematous pustulosis (AGEP), including cases with visceral involvement and/or requiring skin grafts.

Monitor patients for signs and symptoms of SCARs such as fever, flu-like symptoms, mucosal lesions, progressive skin rash or lymphadenopathy. Advise patients and caregivers of the signs and symptoms of SCARs.

If a SCAR is suspected, interrupt LUPRON DEPOT-PED. Consult a healthcare provider with expertise in the diagnosis and management of SCARs. If a diagnosis of SCAR is confirmed permanently discontinue LUPRON DEPOT-PED.

5.5 Pseudotumor Cerebri (Idiopathic Intracranial Hypertension)

Pseudotumor cerebri (idiopathic intracranial hypertension) have been reported in pediatric patients receiving GnRH agonists, including LUPRON DEPOT-PED. Monitor patients for signs and symptoms of pseudotumor cerebri, including headache, papilledema, blurred vision, diplopia, loss of vision, pain behind the eye or pain with eye movement, tinnitus, dizziness, and nausea.

6 ADVERSE REACTIONS

The following serious adverse reactions are described here and elsewhere in the label:

- Initial rise in gonadotropin and sex steroid levels [see Warnings and Precautions (5.1)].
- Psychiatric Events [see Warnings and Precautions (5.2)].
- Convulsions [see Warnings and Precautions (5.3)].
- Severe Cutaneous Adverse Reactions (SCARs) [see Warnings and Precautions (5.4)]
- Pseudotumor Cerebri (Idiopathic Intracranial Hypertension) [see Warnings and Precautions (5.5)]

6.1 Clinical Trials Experience

Because clinical studies are conducted under widely varying conditions, adverse reaction rates observed in the clinical studies of a drug cannot be directly compared to rates in the clinical studies of another drug and may not reflect the rates observed in practice.

LUPRON DEPOT-PED for 1-month administration

LUPRON DEPOT-PED 1-month administration was evaluated in a pivotal, open label, multicenter study in which 55 (49 female and 6 male) pediatric patients with central precocious puberty were enrolled. The age ranged from 1 to 8 years of age at the beginning of treatment; the mean age for females was 6.8 years (range: 1 to 9 years) and the mean age for males was 7.5 years (range: 4 to 9 years); 61.8% were Caucasian; 20% Black; 1.8% Oriental; and 16.4% Hispanic.

Adverse reactions that occurred in ≥2% of patients are shown in Table 2.

Table 2. Adverse Reactions Occurring in ≥2% in Pediatric Patients with CPP Receiving
LUPRON DEPOT-PED 1-month
 | % of Patients (N = 421)
Injection Site Reactions Including Abscess* | 9
Emotional Lability | 5
Headache | 3
General Pain | 3
Acne/Seborrhea | 3
Rash Including Erythema Multiforme | 3
Vaginitis/Vaginal Bleeding/Vaginal Discharge | 3
Vasodilation | 2
* Most events were mild or moderate in severity.

Less Common Adverse Reactions

The following adverse reactions were reported in less than 2% of the patients and are listed below by body system.

Body as a Whole – aggravation of preexisting tumor and decreased vision, allergic reaction, body odor, fever, flu syndrome, hypertrophy, infection;

Cardiovascular System – bradycardia, hypertension, peripheral vascular disorder, syncope; Digestive System – constipation, dyspepsia, dysphagia, gingivitis, increased appetite, nausea/vomiting;

Endocrine System – accelerated sexual maturity, feminization, goiter;

Hemic and Lymphatic System – purpura;

Metabolic and Nutritional Disorders – growth retarded, peripheral edema, weight gain; Musculoskeletal System – arthralgia, joint disorder, myalgia, myopathy;

Nervous System – hyperkinesia, somnolence;

Psychiatric System – depression, nervousness;

Respiratory System – asthma, epistaxis, pharyngitis, rhinitis, sinusitis;

Integumentary System (Skin and Appendages) – alopecia, hair disorder, hirsutism, leukoderma, nail disorder, skin hypertrophy;

Urogenital System – cervix disorder/neoplasm, dysmenorrhea, gynecomastia/breast disorders, menstrual disorder, urinary incontinence.

Laboratory: The following laboratory events were reported as adverse reactions: antinuclear antibody present and increased sedimentation rate.

LUPRON DEPOT-PED for 3-month administration

LUPRON DEPOT-PED for 3-month administration was evaluated in a pivotal, open-label, multicenter, clinical study with 84 randomized pediatric patients with central precocious puberty; 76 (90.5%) were females and 8 (9.5%) were males. The age ranged from 1 to 11 years age at the beginning of treatment; 80/84 (95.2%) were 5 years or older, and female patients were younger than male; the mean age for 11.25 mg and 30 mg groups for females was 7.6 and 7.7 years, and for males 9.3 and 9.4 years, respectively; 58.3% were Caucasian; 22.6% were Black; 7.1% were Asian; 1.2% were Native Hawaiian or Other Pacific Islander; and 10.7% were Multi-race.

Adverse reactions that occurred in ≥2% of patients are shown in Table 3.

Table 3. Adverse Reactions Occurring in ≥2% in Pediatric Patients with CPP
Receiving LUPRON DEPOT-PED for 3-month administration.
 | % 11.25 mg every 3 Months N=42 | % 30 mg every 3 Months N=42 | % Overall N = 84
Injection site pain | 19 | 21 | 20
Weight increased | 7 | 7 | 7
Headache | 2 | 7 | 5
Mood altered | 5 | 5 | 5
Injection site swelling | 2 | 2 | 2

Less Common Adverse Reactions

The following adverse reactions were reported in one patient and are listed below by system organ class:

Gastrointestinal Disorders – abdominal pain, nausea;

General Disorders and Administration Site Conditions – asthenia, gait disturbance, injection site abscess sterile, injection site hematoma, injection site induration, injection site warmth, irritability;

Metabolic and Nutritional Disorders – decreased appetite, obesity;

Musculoskeletal and Connective Tissue Disorders - musculoskeletal pain, pain in extremity; Nervous System Disorders – dizziness;

Psychiatric Disorders – crying, tearfulness;

Respiratory, Thoracic and Mediastinal Disorders – cough;

Skin and Subcutaneous Tissue Disorders – hyperhidrosis;

Vascular Disorders – pallor.

LUPRON DEPOT-PED for 6-month administration

LUPRON DEPOT-PED for 6-month administration was evaluated in an open-label, multicenter, clinical study with 45 pediatric patients with central precocious puberty; 41 (91%) were females and 4 (9%) were males. The baseline age ranged from 4 to 10 years. There were 30 (67%) Caucasian; 7 (16%) Black; and 1 (2%) Asian.

Adverse reactions that occurred in ≥4% of all patients are shown in Table 4.

Table 4. Adverse Reactions Occurring in ≥4% in Pediatric Patients with CPP
Receiving LUPRON DEPOT-PED for 6-month administration.
 | Total (N = 45) n (%)
Injection Site Reactions a | 35 (78%)
Headache b | 15 (33%)
Psychiatric Events c | 10 (22%)
Abdominal Pain d | 8 (18%)
Diarrhea e | 7 (16%)
Hemorrhage f | 6 (13%)
Nausea and Vomiting | 6 (13%)
Pyrexia | 6 (13%)
Pruritus g | 5 (11%)
Pain in extremity | 4 (9%)
Rash | 3 (7%)
Back Pain | 3 (7%)
Ligament sprain | 3 (7%)
Weight increased | 3 (7%)
Fracture h | 2 (4%)
Breast tenderness i | 2 (4%)
Insomnia j | 2 (4%)
Chest pain | 2 (4%)
Hyperhidrosis | 2 (4%)
a Injection site reactions includes the preferred terms injection site pain, injection site erythema, injection site
reaction, injection site warmth, injection site bruising, injection site discomfort, and injection site swelling
b^- Headache includes the preferred terms headache and cluster headache
c Psychiatric events includes the preferred terms affect lability, affective disorder, aggression, crying,
depressed mood, disruptive mood dysregulation disorder, hallucination auditory, mood altered,
mood swings, and trichotillomania
d Abdominal pain includes the preferred terms abdominal pain, abdominal pain upper, and abdominal discomfort
e Diarrhea includes the preferred terms gastroenteritis and diarrhea
f Hemorrhage includes the preferred terms contusion, epistaxis, hematochezia, and injection site bruising
g Pruritus includes the preferred terms pruritus, vulvovaginal pruritus, nasal pruritus
h Fracture includes the preferred terms ankle fracture and tibia fracture
i Breast tenderness includes the preferred terms breast pain and breast tenderness
j Insomnia includes the preferred terms initial insomnia and insomnia

6.2 Postmarketing Experience

The following adverse reactions have been identified during post-approval use of LUPRON DEPOT-PED or GnRH agonists in pediatric patients. Because these reactions are reported voluntarily from a population of uncertain size, it is not always possible to reliably estimate their frequency or establish a causal relationship to drug exposure.

Allergic reactions: anaphylactic, rash, urticaria, and photosensitivity reactions.

General disorders and administration site conditions: chest pain, weight increase, decreased appetite, fatigue, injection site reactions including induration, abscess, and necrosis.

Laboratory Abnormalities: decreased WBC.

Metabolic: diabetes mellitus.

Musculoskeletal and Connective Tissue: tenosynovitis-like symptoms, severe muscle pain, arthralgia, epiphysiolysis, muscle spasms, myalgia.

Published literature and postmarketing reports indicate that bone mineral density may decrease during GnRH therapy in pediatric patients with central precocious puberty. Published studies indicate that after discontinuation of therapy, subsequent bone mass accrual is preserved and peak bone mass in late adolescence does not seem to be affected.

Neurologic: neuropathy peripheral, convulsion, insomnia, pseudotumor cerebri (idiopathic intracranial hypertension).

Psychiatric Disorders: emotional lability, such as crying, irritability, impatience, anger, and aggression. Depression, including rare reports of suicidal ideation and attempt. Many, but not all, of these patients had a history of psychiatric illness or other comorbidities with an increased risk of depression.

Reproductive System: vaginal bleeding, breast enlargement.

Respiratory: dyspnea.

Skin and Subcutaneous Tissue: flushing, hyperhidrosis, erythema multiforme, bullous dermatitis, dermatitis exfoliative, drug reaction with eosinophilia and systemic symptoms, Stevens-Johnson syndrome and toxic epidermal necrolysis, and acute generalized exanthematous pustulosis.

Vascular Disorders: hypertension, hypotension.

7 DRUG INTERACTIONS

7.1 Drug Interactions

No pharmacokinetic-based drug-drug interaction studies have been conducted with LUPRON DEPOT-PED [see Clinical Pharmacology (12.3)].

7.2 Drug-Laboratory Test Interactions

Administration of LUPRON DEPOT-PED in therapeutic doses results in suppression of the pituitary-gonadal system. Therefore, diagnostic tests of pituitary gonadotropic and gonadal functions conducted during treatment and up to six months after discontinuation of LUPRON DEPOT-PED may be affected. Normal pituitary-gonadal function is usually restored within six months after treatment with LUPRON DEPOT-PED is discontinued.

8 USE IN SPECIFIC POPULATIONS

8.1 Pregnancy

Risk Summary

LUPRON DEPOT-PED is contraindicated in pregnancy [see Contraindications (4)].

LUPRON DEPOT-PED may cause fetal harm, when administered to a pregnant woman, based on findings from animal studies and the drug’s mechanism of action [see Clinical Pharmacology (12.1)]. The available data from published clinical studies and case reports and from the pharmacovigilance database on exposure to LUPRON DEPOT-PED during pregnancy are insufficient to assess the risk of major birth defects, miscarriage, or adverse maternal or fetal outcomes. Based on animal reproduction studies, LUPRON DEPOT-PED may be associated with an increased risk of pregnancy complications, including early pregnancy loss and fetal harm. In animal reproduction studies, subcutaneous administration of leuprolide acetate to rabbits during the period of organogenesis caused embryo-fetal toxicity, decreased fetal weights and a dose-dependent increase in major fetal abnormalities in animals at doses less than the recommended human dose based on body surface area using an estimated daily dose. A similar rat study also showed increased fetal mortality and decreased fetal weights but no major fetal abnormalities at doses less than the recommended human dose based on body surface area using an estimated daily dose (see Data).

The estimated background risk of major birth defects and miscarriage for the indicated population is unknown. In the US general population, the estimated background risk of major birth defects and miscarriage in clinically recognized pregnancies is 2% - 4% and 15% -20%, respectively.

Data

Animal Data

When administered on day 6 of pregnancy at test dosages of 0.00024 mg/kg, 0.0024 mg/kg, and 0.024 mg/kg (doses less than the recommended human dose) to rabbits, leuprolide acetate produced a dose-related increase in malformations comprised primarily of segmental and fusion defects of the skeleton and skull. Similar studies in rats failed to demonstrate an increase in fetal malformations. There was increased fetal mortality and decreased fetal weights with the two higher doses of leuprolide acetate in rabbits and with the highest dose (0.024 mg/kg) in rats.

8.2 Lactation

Risk Summary

There are no data on the presence of leuprolide acetate in either animal or human milk, the effects on the breastfed infants, or the effects on milk production. The developmental and health benefits of breastfeeding should be considered along with the mother’s clinical need for LUPRON DEPOT-PED and any potential adverse effects on the breastfed infant from LUPRON DEPOT-PED or from the underlying maternal condition.

8.3 Females and Males of Reproductive Potential

Pregnancy Testing

Exclude pregnancy in women of reproductive potential prior to initiating LUPRON DEPOT-PED if clinically indicated [see Use in Specific Populations (8.1)].

Contraception

Females

LUPRON DEPOT-PED may cause embryo-fetal harm when administered during pregnancy. LUPRON DEPOT-PED is not a contraceptive. If contraception is indicated, advise females of reproductive potential to use a non-hormonal method of contraception during treatment with LUPRON DEPOT-PED [see Use in Specific Populations (8.1)].

Infertility

Based on its pharmacodynamic effects of decreasing secretion of gonadal steroids, fertility is expected to be decreased while on treatment with LUPRON DEPOT-PED. Clinical and pharmacologic studies in adults (>18 years) with leuprolide acetate and similar analogs have shown reversibility of fertility suppression when the drug is discontinued after continuous administration for periods of up to 24 weeks [see Clinical Pharmacology (12.2)].

There is no evidence that pregnancy rates are affected following discontinuation of LUPRON DEPOT-PED.

Animal studies (prepubertal and adult rats and monkeys) with leuprolide acetate and other GnRH analogs have shown functional recovery of fertility suppression.

8.4 Pediatric Use

The safety and effectiveness of LUPRON DEPOT-PED for the treatment of CPP has been established in pediatric patients 1 years of age and older. Use of LUPRON DEPOT-PED for this indication is supported by evidence from two pivotal, open label clinical studies of 139 pediatric patients with central precocious puberty with an age range of 1 to 11 years [see Clinical Studies (14)]. The safety and effectiveness of LUPRON DEPOT-PED have not been established in pediatric patients less than 1 year old.

10 OVERDOSAGE

No specific antidotes for LUPRON DEPOT-PED are known. Contact Poison Control (1-800-222-1222) for latest recommendations.

In cases of overdosage, standard of care monitoring and management principles should be followed.

11 DESCRIPTION

LUPRON DEPOT-PED contains active ingredient, leuprolide, in the form of acetate salt, a gonadotropin-releasing hormone (GnRH) agonist. It is a synthetic nonapeptide analog of naturally occurring gonadotropin-releasing hormone (GnRH or LH-RH). The analog possesses greater potency than the natural hormone. The chemical name of leuprolide acetate is 5-oxo-L-prolyl-L-histidyl-L-tryptophyl-L-seryl-L-tyrosyl-D-leucyl-L-leucyl-L-arginyl-N-ethyl-L-prolinamide acetate, which has molecular formula of C59H84N16O12.(C2H4O2)n, n=1 or 2, with the following structural formula:

LUPRON DEPOT-PED for 1-month administration

LUPRON DEPOT-PED is available in a prefilled dual-chamber single-dose syringe containing sterile lyophilized microsphere powder incorporated in a biodegradable lactic acid/glycolid acid copolymer which, when mixed with diluent, becomes a suspension for intramuscular injection. When mixed with 1 milliliter of accompanying diluent, LUPRON DEPOT-PED for 1-month administration is administered as a single-dose intramuscular injection.

The front chamber of LUPRON DEPOT-PED 7.5 mg, 11.25 mg, and 15 mg a prefilled dual-chamber syringe contains leuprolide acetate (7.5 mg equivalent to 6.83-7.15 mg leuprolide / 11.25 mg equivalent to 10.24 – 10.72 mg leuprolide / 15 mg equivalent to 13.65 – 14.30 mg leuprolide), purified gelatin (1.3/1.95/2.6 mg), DL-lactic and glycolic acids copolymer (66.2/99.3/132.4 mg), and D-mannitol (13.2/19.8/26.4 mg). The second chamber of diluent contains carboxymethylcellulose sodium (5 mg), D-mannitol (50 mg), polysorbate 80 (1 mg), water for injection, USP, and glacial acetic acid, USP to control pH.

LUPRON DEPOT-PED for 3-month administration

LUPRON DEPOT-PED 11.25 mg or 30 mg for 3-month administration is available in a prefilled dual-chamber single-dose syringe containing sterile lyophilized microsphere powder incorporated in a biodegradable lactic acid/glycolid acid copolymer which, when mixed with diluent, becomes a suspension for intramuscular injection. When mixed with 1.5 milliliters of accompanying diluent, LUPRON DEPOT-PED for 3-month administration is administered as a single-dose intramuscular injection.

The front chamber of LUPRON DEPOT-PED 11.25 mg for 3-month administration prefilled dual-chamber syringe contains leuprolide acetate (11.25 mg, equivalent to 10.24 - 10.72 mg leuprolide), D-mannitol (19.45 mg), and polylactic acid (99.3 mg). The second chamber of diluent contains carboxymethylcellulose sodium (7.5 mg), D-mannitol (75.0 mg), polysorbate 80 (1.5 mg), water for injection, USP, and glacial acetic acid, USP to control pH.

The front chamber of LUPRON DEPOT-PED 30 mg for 3-month administration prefilled dual-chamber syringe contains leuprolide acetate (30 mg, equivalent to 27.30 - 28.59 mg leuprolide), D-mannitol (51.9 mg), and polylactic acid (264.8 mg). The second chamber of diluent contains carboxymethylcellulose sodium (7.5 mg), D-mannitol (75.0 mg), polysorbate 80 (1.5 mg), water for injection, USP, and glacial acetic acid, USP to control pH.

LUPRON DEPOT-PED for 6-month administration

LUPRON DEPOT-PED 45 mg for 6-month administration is available in a prefilled dual-chamber syringe containing sterile lyophilized microspheres which, when mixed with diluent, become a suspension intended as an intramuscular injection.

The front chamber of LUPRON DEPOT-PED 45 mg for 6-month administration prefilled dual-chamber syringe contains leuprolide acetate (45 mg, equivalent to 40.95 - 42.89 mg leuprolide), D-mannitol (39.7 mg), polylactic acid (169.9 mg), and stearic acid (10.1 mg). The second chamber of diluent contains carboxymethylcellulose sodium (7.5 mg), D-mannitol (75.0 mg), polysorbate 80 (1.5 mg), water for injection, USP, and glacial acetic acid, USP to control pH.

12 CLINICAL PHARMACOLOGY

12.1 Mechanism of Action

Leuprolide acetate, a GnRH agonist, acts as a potent inhibitor of gonadotropin secretion (LH and follicle stimulating hormone (FSH)) when given continuously in therapeutic doses.

12.2 Pharmacodynamics

Following an initial stimulation of GnRH receptors, chronic administration of leuprolide acetate results in downregulation of GnRH receptors, reduction in release of LH and FSH, and consequent suppression of ovarian and testicular production of estradiol and testosterone, respectively. This inhibitory effect is reversible upon discontinuation of drug therapy.

12.3 Pharmacokinetics

Absorption

LUPRON DEPOT-PED for 1-month administration

Following a single LUPRON DEPOT-PED 7.5 mg for 1-month administration to adult patients, mean peak leuprolide plasma concentration was almost 20 ng/mL at 4 hours and then declined to 0.36 ng/mL at 4 weeks. However, intact leuprolide and an inactive major metabolite could not be distinguished by the assay which was employed in the study. Nondetectable leuprolide plasma concentrations have been observed during chronic LUPRON DEPOT-PED 7.5 mg administration, but testosterone levels appear to be maintained at castrate levels.

In a study of pediatric patients with CPP, doses of 7.5 mg, 11.25 mg and 15.0 mg of LUPRON DEPOT-PED were given every 4 weeks. In 22 pediatric patients, trough leuprolide plasma levels were determined according to weight categories as summarized below:

Patient Weight Range (kg) | Group Weight Average (kg) | Dose (mg) | Trough Plasma Leuprolide Level Mean ±SD (ng/mL)*
20.2 - 27.0 | 22.7 | 7.5 | 0.77±0.033
28.4 - 36.8 | 32.5 | 11.25 | 1.25±1.06
39.3 - 57.5 | 44.2 | 15.0 | 1.59±0.65
* Group average values determined at Week 4 immediately prior to leuprolide injection. Drug levels at 12 and 24 weeks were similar to respective 4 week levels.

LUPRON DEPOT-PED for 3-month administration

Following a single LUPRON DEPOT-PED 11.25 mg or 30 mg for 3-month administration to pediatric patients with CPP, leuprolide concentrations increased with increasing dose with mean peak leuprolide plasma concentration of 19.1 and 52.5 ng/mL at 1 hour for the 11.25 and 30 mg dose levels, respectively. The concentrations then declined to 0.08 and 0.25 ng/mL at 2 weeks after dosing for the 11.25 and 30 mg dose levels. Mean leuprolide plasma concentration remained constant from month 1 to month 3 for both 11.25 and 30 mg doses. The mean leuprolide concentrations 3 months after the first and second injections were similar indicating no accumulation of leuprolide from repeated administration.

LUPRON DEPOT-PED for 6-month administration

Following a single injection of LUPRON DEPOT-PED 45 mg for 6-month administration in 20 pediatric patients with CPP, mean peak plasma concentration increased rapidly to 15.7 ng/mL 1 hour post-dose. Following the initial rise, mean leuprolide plasma concentration declined to 0.03 ng/mL by Week 24. The mean leuprolide concentrations 6 months after the first and second injections were comparable indicating no accumulation of leuprolide from repeated administration.

Distribution

The mean steady-state volume of distribution of leuprolide following intravenous bolus administration to healthy male subjects was 27 L. In vitro binding to human plasma proteins ranged from 43% to 49%.

Elimination

Metabolism

In healthy male subjects given an intravenous 1 mg bolus of leuprolide the mean systemic clearance was 7.6 L/h, with a terminal elimination half-life of approximately 3 hours based on a two-compartment model.

In rats and dogs, administration of ^14C-labeled leuprolide was shown to be metabolized to smaller inactive peptides; a pentapeptide (Metabolite I), tripeptides (Metabolites II and III) and a dipeptide (Metabolite IV). These fragments may be further catabolized.

The major metabolite (M-I) plasma concentrations measured in 5 prostate cancer patients reached maximum concentration 2 to 6 hours after dosing and were approximately 6% of the peak parent drug concentration. One week after dosing, mean plasma M-I concentrations were approximately 20% of mean leuprolide concentrations.

Excretion

Following administration of LUPRON DEPOT 3.75 mg to 3 patients, less than 5% of the dose was recovered as parent and M-I metabolite in the urine.

Specific Populations

The pharmacokinetics of LUPRON DEPOT-PED has not been determined in patients with hepatic or renal impairment.

Drug-Drug Interactions

No pharmacokinetic-based drug-drug interaction studies have been conducted with LUPRON DEPOT-PED. Leuprolide acetate is a peptide that is not degraded by cytochrome P-450 enzymes; hence, drug interactions associated with cytochrome P-450 enzymes would not be expected to occur.

13 NONCLINICAL TOXICOLOGY

13.1 Carcinogenesis, Mutagenesis, Impairment of Fertility

A two-year carcinogenicity study was conducted in rats and mice. In rats, a dose-related increase of benign pituitary hyperplasia and benign pituitary adenomas was noted at 24 months when the drug was administered subcutaneously at high daily doses (0.6 to 4 mg/kg). There was a significant but not dose-related increase of pancreatic islet-cell adenomas in females and of testicular interstitial cell adenomas in males (highest incidence in the low dose group). In mice, no leuprolide acetate-induced tumors or pituitary abnormalities were observed at a dose as high as 60 mg/kg for two years.

Mutagenicity studies have been performed with leuprolide acetate using bacterial and mammalian systems. These studies provided no evidence of a mutagenic potential.

14 CLINICAL STUDIES

14.1 LUPRON DEPOT-PED for 1-month administration

The efficacy of LUPRON DEPOT-PED was evaluated in a pivotal open-label, multicenter clinical trial (NCT00660010) in which 55 pediatric patients with central precocious puberty (49 females and 6 males, naïve to previous GnRHa treatment) were treated with LUPRON DEPOT-PED 1-month formulations until age was appropriate for entry into puberty (see treatment period data below)and a subset of 40 patients were then followed post-treatment (see follow-up period data below). The mean ± SD age at the start of treatment was 7 ± 2 years and the duration of treatment was 4 ± 2 years. Study drug was administered intramuscularly (IM) every 28 days, with incremental adjustments of 3.75mg at each clinic visit, if necessary based on clinical and laboratory results. During the follow-up period, GnRHa stimulation test was performed every 6 months until a pubertal response was observed.

During the treatment period, LUPRON DEPOT-PED suppressed gonadotropins and sex steroids to prepubertal levels. Suppression of peak stimulated LH concentrations to < 1.75 mIU/mL was achieved in 96% of patients by month 1. Five patients required increased doses of study drug to achieve or retain LH suppression. The number and percentage of patients with suppression of peak stimulated LH < 1.75 mIU/mL and mean ± SD peak stimulated LH over time is shown in Table 5. Six months after the treatment period was finished, the mean peak stimulated LH was 20.6 ± SD 13.7 mIU/mL (n=30).

The following effects have been noted with the chronic administration of leuprolide: cessation of menses (in girls), normalization and stabilization of linear growth and bone age advancement, stabilization of clinical signs and symptoms of puberty.

Table 5. The number and percentage of patients with peak
stimulated LH < 1.75 mIU/mL and Mean (SD) peak LH at each
clinic visit
Weeks on Study | n with peak stimulated LH < 1.75 mIU/mL/ N with a LH measurement for that week |  | Mean (SD) peak LH
 | n/N | %
Baseline | 0/55 | 0% | 35.0 (21.32)
Week 4 | 53/55 | 96.4% | 0.8 (0.57)
Week 12 | 48/54 | 88.9% | 1.1 (1.77)
Week 24 | 48/53 | 90.6% | 0.8 (0.79)
Week 36 | 51/54 | 94.4% | 0.6 (0.43)
Week 48 | 51/54 | 94.4% | 0.6 (0.47)
Week 72 | 52/52 | 100% | 0.5 (0.30)
Week 96 | 46/46 | 100% | 0.4 (0.33)
Week 120 | 40/40 | 100% | 0.4 (0.27)
Week 144 | 36/36 | 100% | 0.4 (0.24)
Week 168 | 27/28 | 96.4% | 1.2 (4.58)
Week 216 | 18/19 | 94.7% | 0.5 (0.90)
Week 240 | 16/17 | 94.1% | 0.4 (0.62)
Week 264 | 14/15 | 95.3% | 0.4 (0.41)
Week 288 | 11/11 | 100% | 0.3 (0.22)
Week 312 | 9/9 | 100% | 0.4 (0.20)
Week 336 | 6/6 | 100% | 0.3 (0.10)
Week 360 | 6/6 | 100% | 0.3 (0.13)
Week 384 | 5/5 | 100% | 0.2 (0.10)
Week 408 | 3/3 | 100% | 0.2 (0.09)
Week 432 | 2/2 | 100% | 0.3 (0.04)
Week 456 | 2/2 | 100% | 0.2 (0.04)
Week 480 | 1/1 | 100% | 0.2 (NA)
Week 504 | 1/1 | 100% | 0.2 (NA)

Suppression (defined as regression or no change) of the clinical/physical signs of puberty was achieved in most patients. In females, suppression of breast development ranged from 66.7 to 90.6% of patients during the first 5 years of treatment. The mean stimulated estradiol was 15.1 pg/mL at baseline, decreased to the lower level of detection (5.0 pg/mL) by Week 4 and was maintained there during the first 5 years of treatment. In males, suppression of genitalia development ranged from 60% to 100% of patients during the first 5 years of treatment. The mean stimulated testosterone was 347.7 ng/dL at baseline and was maintained at levels no greater than 25.3 ng/dL during the first 5 years of treatment.

A “flare effect” of transient bleeding or spotting during the first 4 weeks of treatment was observed in 19.4% (7/36) females who had not reached menarche at baseline. After the first 4 weeks and for the remainder of the treatment period, no patients reported menstrual-like bleeding, and only rare spotting was noted.

The mean ratio of bone age to chronological age decreased from 1.5 at baseline to 1.1 by end of treatment. The mean height standard deviation z-score changed from 1.6 at baseline to 0.7 at the end of the treatment phase.

Thirty five (35) females and 5 males participated in a post-treatment follow-up period to assess reproductive function (in females) and final height. At 6 months post-treatment, most patients reverted to pubertal levels of LH (87.9%) and clinical signs of resumption of pubertal progression were evident with increase in breast development in girls (66.7%) and increase in genitalia development in boys (80%).

After stopping treatment, regular menses were reported for all female patients who reached 12 years of age during follow-up; mean time to menses was approximately 1.5 years; mean age of onset of menstruation after stopping treatment was 12.9 years.

Of the 40 patients evaluated in the follow-up, 33 were observed until they reached final or near-final adult height. These patients had a mean increase in final adult height compared to baseline predicted adult height. The mean final adult height standard deviation score was -0.2.

14.2 LUPRON DEPOT-PED for 3-month administration

The efficacy was evaluated in a 6-month, randomized, open-label clinical study of LUPRON DEPOT-PED 3-Month formulations (NCT00667446). 84 patients (76 female, 8 male) between 1 and 11 years of age received the LUPRON DEPOT-PED 11.25 mg or 30 mg for 3-month administration formulation. Each dose group had an equal number of treatment-naïve patients who had pubertal LH levels and patients previously treated with GnRHa therapies who had prepubertal LH levels at the time of study entry. The percentage of patients with suppression of peak-stimulated LH to < 4.0 mIU/mL, as determined by assessments at months 2, 3 and 6, is 78.6% in the 11.25 mg dose and 95.2% in the 30 mg dose as shown in Table 6.

Table 6. Suppression of Peak-Stimulated LH from Month 2 Through Month 6
 | LUPRON DEPOT-PED 11.25 mg every 3 Months |  |  | LUPRON DEPOT-PED 30 mg every 3 Months
Parameter | Naïve N = 21 | Prev Trta N = 21 | Total N = 42 | Naïve N = 21 | Prev Trta N = 21 | Total N = 42
Percent with Suppression | 76.2 | 81.0 | 78.6 | 90.5 | 100 | 95.2
2-sided 95% CI | 52.8, 91.8 | 58.1, 94.6 | 63.2, 89.7 | 69.6, 98.8 | 83.9, 100 | 83.8, 99.4

a. Previously treated with GnRHa for at least 6 months prior to enrollment in pivotal Study L-CP07-167.

The mean peak stimulated LH levels for all visits are shown by dose and subgroup (naïve vs. previously treated patients) in Figures 8 and 9.

Figure 8. Mean Peak Stimulated LH for LUPRON DEPOT-PED 11.25 mg for 3-month administration

Figure 9. Mean Peak Stimulated LH for LUPRON DEPOT-PED

30 mg for 3-month administration

For the LUPRON DEPOT-PED 11.25 mg dose for 3-month administration, 93% (39/42) of patients and for LUPRON DEPOT-PED 30 mg dose for 3-month administration, 100% (42/42) of patients had sex steroid (estradiol or testosterone) suppressed to prepubertal levels at all visits. Clinical suppression of puberty in female patients was observed in 29 of 32 (90.6%) and 28 of 34 (82.4%) of patients in the 11.25 mg and 30 mg groups, respectively, at month 6. Clinical suppression of puberty in males was observed in 1 of 2 (50%) and 2 of 5 (40%) patients in the 11.25 mg and 30 mg groups, respectively, at month 6. In patients with complete data for bone age, 29 of 33 (88%) in the 11.25 mg group and 30 of 40 in the 30 mg group (75%) had a decrease in the ratio of bone age to chronological age at month 6 compared to screening.

14.3 LUPRON DEPOT-PED for 6-month administration

The safety and efficacy of LUPRON DEPOT-PED 6-Month formulation was evaluated in an open-label, single-arm, multicenter, clinical trial (NCT03695237).

In the clinical trial, 27 pediatric patients with central precocious puberty (24 females and 3 males) naïve to previous GnRH agonist treatment and 18 pediatric patients with central precocious puberty (17 females and 1 males) previously treated with GnRH agonist therapy (including 1-,3-, 6- and 12- month) received LUPRON DEPOT-PED 45 mg. LUPRON DEPOT-PED 45 mg was administered as an intramuscular injection at two intervals 24 weeks apart.

The primary efficacy endpoint of percentage of patients with suppression of peak-stimulated LH to < 4.0 mIU/mL at Week 24 was achieved in 39/45 (86.7%) patients (Table 7). Of the patients previously treated with other GnRHa formulations 94.4% remained suppressed at Week 24.

Table 7. Suppression of Peak-Stimulated GnRHa-Stimulated LH at Week 24
 | LUPRON DEPOT-PED 45 mg
Parameter | Naïve N = 27 | Prev Trta N = 18 | Total N =45
Percent with Suppression, n (%) | 22 (81.5) | 17 (94.4) | 39 (86.7)
95% CI | 61.9, 93.7 | 72.7, 99.9 | 73.2, 95.0

1. Previously treated with GnRHa for at least 6 months prior to enrollment in pivotal Study M16-904

The mean peak stimulated LH levels decreased from 17.4 mIU/mL in treatment-naïve patients and from 2.1 mIU/ML in previously treated patients at baseline to 1.6 mIU/mL and 1.5 mIU/mL respectively at Week 4. The levels remained suppressed for all visits up to Week 48.

The proportion of female patients with suppression of basal estradiol to <20 pg/mL was 97.4% at Week 24 and 100% at Week 48. The proportion of male patients with suppression of testosterone to <30 ng/dL was 100% at Weeks 24 and 48. Suppression (defined as regression or no change) of the physical signs of puberty was achieved in most patients.

In patients with complete data for bone age, 40 of 45 (88.9%) and 42 of 45 (93.3%) had a decrease in the ratio of bone age to chronological age at Weeks 24 and 48, respectively, compared to baseline.

In the extension part of the study (Weeks 49 to 144), 4 of 45 enrolled patients discontinued due to lack of efficacy. Twenty-three patients had complete data available through Week 144; LH suppression was maintained in all 23 patients.

16 HOW SUPPLIED/STORAGE AND HANDLING

How Supplied

LUPRON DEPOT-PED for depot suspension is supplied in a single dose, prefilled dual-chamber syringe containing a white lyophilized powder and a colorless diluent for reconstitution as follows (Table 8):

Table 8. LUPRON DEPOT-PED Product Presentations
LUPRON DEPOT-PED 7.5 mg, 11.25 mg, or 15 mg for 1-Month Administration
Kit Type | Strength | NDC Number
1-month kit | 7.5 mg | NDC 0074-2108-03
 | 11.25 mg | NDC 0074-2282-03
 | 15 mg | NDC 0074-2440-03
LUPRON DEPOT-PED 11.25 mg or 30 mg for 3-Month Administration
3-month kit | 11.25 mg | NDC 0074-3779-03
 | 30 mg | NDC 0074-9694-03
LUPRON DEPOT-PED 45 mg for 6-Month Administration
6-month kit | 45 mg | NDC 0074-3575-01

Each kit contains:

- one single-dose, prefilled dual-chamber syringe containing 23 gauge 1½ inch needle with LuproLoc® safety device
- one plunger
- two alcohol swabs
- population, dose and frequency confirmation insert
- a complete prescribing information enclosure

Storage and Handling

Prior to reconstitution, store at 20°C to 25°C (68°F to 77°F); excursions permitted to 15°C to 30°C (59°F to 86°F) [See USP Controlled Room Temperature].

After reconstitution, use immediately [see Dosage and Administration (2.5, 2.6)].

17 PATIENT COUNSELING INFORMATION

Advise the patient to read the FDA-approved patient labeling (Medication Guide).

Symptoms After Initial LUPRON DEPOT-PED Administration

Inform patients and caregivers that during the early phase of therapy with LUPRON DEPOT-PED, gonadotropins and sex steroids rise above baseline because of the initial stimulatory effect of the drug. Therefore, an increase in clinical signs and symptoms of puberty may be observed. Instruct patients and caregivers to notify the physician if these symptoms continue beyond the second month after LUPRON DEPOT-PED administration [see Warnings and Precautions (5.1)].

Psychiatric Events

Inform patients and caregivers that psychiatric events have been reported in patients taking GnRH agonists, including leuprolide acetate. Events include emotional lability, such as crying, irritability, impatience, anger, and aggression. Instruct patients and caregivers to monitor for development or worsening of psychiatric symptoms including depression during treatment with LUPRON DEPOT-PED [see Warnings and Precautions (5.2)].

Convulsions

Inform patients and caregivers that reports of convulsions have been observed in patients receiving GnRH agonists, including leuprolide acetate. Patients with a history of seizures, epilepsy, cerebrovascular disorders, central nervous system anomalies or tumors, and patients on concomitant medications that have been associated with convulsions may be at increased risk [see Warnings and Precautions (5.3)].

Severe Cutaneous Adverse Reactions

Inform patients and/or caregivers that severe cutaneous adverse reactions (SCARs) may occur during treatment with LUPRON DEPOT-PED. Advise patients and/or caregivers to stop LUPRON DEPOT-PED and immediately contact their healthcare provider if they experience signs or symptoms of SCARs [see Warnings and Precautions (5.4)].

Pseudotumor Cerebri (Idiopathic Intracranial Hypertension)

Inform patients and caregivers that reports of pseudotumor cerebri (idiopathic intracranial hypertension) have been observed in pediatric patients receiving GnRH agonists, including LUPRON DEPOT-PED. Advise patients and caregivers to monitor for headache and vision issues such as blurred vision, double vision, loss of vision, pain behind the eye or pain with eye movement, ringing in the ears, dizziness, and nausea. Advise patients and caregivers to contact their healthcare provider if the patient develops any of these symptoms [see Warnings and Precautions (5.5)].

Injection Site Reactions

Inform patients and caregivers that injection site related adverse reactions may occur such as transient burning/stinging, pain, bruising, redness, induration, abscess, and necrosis. Advise patients to contact their healthcare provider if they experience rash or severe injection site reactions [see Adverse Reactions (6.1)].

Pregnancy

LUPRON DEPOT-PED is contraindicated in pregnancy. If the patient becomes pregnant while taking the drug, the patient should be informed of the potential risk to the fetus [see Use in Specific Populations (8.1)].

Compliance with the Dosing Schedule

Inform caregivers about the importance of adherence to the LUPRON DEPOT-PED dosing schedule [see Dosage and Administration (2.2, 2.3, 2.4)].

Manufactured for
AbbVie Inc.
North Chicago, IL 60064
by Takeda Pharmaceutical Company Limited
Osaka, Japan 540-8645
LUPRON DEPOT PED and its design are trademarks of AbbVie Endocrine Inc.
© 2025 AbbVie. All rights reserved.

20097738

MEDICATION GUIDE
LUPRON DEPOT-PED® (loo-pron depo peed)
(leuprolide acetate for depot suspension)

What is the most important information I should know about LUPRON DEPOT-PED?

- During the first 2 to 4 weeks of treatment, LUPRON DEPOT-PED can cause an increase in some hormones. During this time you may notice more signs of puberty in your child, including vaginal bleeding. Call your doctor if these signs continue after the second month of treatment with LUPRON DEPOT-PED.
- Some people taking gonadotropin releasing hormone (GnRH) agonists like LUPRON DEPOT-PED have had new or worsened mental (psychiatric) problems. Mental (psychiatric) problems may include emotional symptoms such as:
  ◦ crying
  ◦ irritability
  ◦ restlessness (impatience)
  ◦ anger
  ◦ acting aggressive

Call your child’s doctor right away if your child has any new or worsening mental symptoms or problems while taking LUPRON DEPOT-PED.

- Some people taking GnRH agonists like LUPRON DEPOT-PED have had seizures. The risk of seizures may be higher in people who:
  ◦ have a history of seizures
  ◦ have a history of epilepsy
  ◦ have a history of brain or brain vessel (cerebrovascular) problems or tumors
  ◦ are taking a medicine that has been connected to seizures such as bupropion or selective serotonin reuptake inhibitors (SSRIs)

Seizures have also happened in people who have not had any of these problems. Call your child’s doctor right away if your child has a seizure while taking LUPRON DEPOT-PED.

- Severe cutaneous (skin) adverse reactions may happen during treatment with GnRH agonists like LUPRON DEPOT-PED. Stop LUPRON DEPOT-PED and call your child’s doctor right away if your child has any of the following signs or symptoms during treatment with LUPRON DEPOT-PED:

- skin rash or acne
- dry skin
- itching
- blisters on your skin
- redness or swelling of your face, hands, or soles of your feet

- blisters or sores in your mouth
- peeling of your skin
- fever
- muscle or joint aches
- swollen glands

- Increased pressure in the fluid around the brain can happen in children taking gonadotropin releasing hormone (GnRH) agonist medicines including LUPRON DEPOT-PED. Call your child’s doctor right away if your child has any of the following symptoms during treatment with LUPRON DEPOT-PED:

- headache
- eye problems, including blurred vision, double vision and decreased eyesight
- eye pain

- ringing in the ears
- dizziness
- nausea

What is LUPRON DEPOT-PED?

- LUPRON DEPOT-PED is an injectable prescription gonadotropin releasing hormone (GnRH) medicine used for the treatment of children with central precocious puberty (CPP).
- It is not known if LUPRON DEPOT-PED is safe and effective in children less than 1 year old.

LUPRON DEPOT-PED should not be taken if your child is:

- allergic to GnRH, GnRH agonist medicines, or any ingredients in LUPRON DEPOT-PED. See the end of this Medication Guide for a complete list of ingredients in LUPRON DEPOT-PED.
- pregnant or becomes pregnant. LUPRON DEPOT-PED can cause birth defects or loss of the baby. If your child becomes pregnant call your doctor.

Before your child receives LUPRON DEPOT-PED, tell their doctor about all of your child’s medical conditions including if they:

- have a history of mental (psychiatric) problems.
- have a history of seizures.
- have a history of epilepsy.
- have a history of brain or brain vessel (cerebrovascular) problems or tumors.
- are taking a medicine that has been connected to seizures such as bupropion or selective serotonin reuptake inhibitors (SSRIs).
- are breastfeeding or plans to breastfeed. It is not known if LUPRON DEPOT-PED passes into the breast milk.

Tell your doctor about all the medicines your child takes, including prescription and over-the-counter medicines, vitamins, and herbal supplements.

How will your child receive LUPRON DEPOT-PED?

- Your child’s doctor should do tests to make sure your child has CPP before treating them with LUPRON DEPOT-PED.
- LUPRON DEPOT-PED is given as a single-dose injection into your child’s muscle each month, every 3 months, or every 6 months by a doctor or trained nurse. Your doctor will decide how often your child will receive the injection.
- Keep all scheduled visits to the doctor. If a scheduled dose is missed, your child may start having signs of puberty again. The doctor will do regular exams and blood tests to check for signs of puberty.

What are the possible side effects of LUPRON DEPOT-PED?
LUPRON DEPOT-PED may cause serious side effects. See “What is the most important information I should know about LUPRON DEPOT-PED?”
The most common side effects of LUPRON DEPOT-PED received 1 time each month include:

- injection site reactions such as pain, swelling, and abscess
- weight gain
- pain throughout body
- headache
- acne or red, itchy, rash, and white scales (seborrhea)
- serious skin rash (erythema multiforme)
- mood changes
- swelling of vagina (vaginitis), vaginal bleeding, and vaginal discharge

The most common side effects of LUPRON DEPOT-PED received every 3 months include:

- injection site reactions such as pain and swelling
- weight gain
- headache
- mood changes

The most common side effects of LUPRON DEPOT-PED received every 6 months include:

- injection site reactions such as pain, and swelling
- headache
- mood changes
- upper stomach pain
- diarrhea
- bleeding

- nausea and vomiting
- fever
- itching
- pain in extremity
- rash
- back pain
- ligament sprain

- weight gain
- fracture
- breast tenderness
- difficulty sleeping
- chest pain
- excessive sweating

These are not all the possible side effects of LUPRON DEPOT-PED. Call your doctor for medical advice about side effects. You may report side effects to FDA at 1-800-FDA-1088.

How should I store LUPRON DEPOT-PED INJECTION?

- Store LUPRON DEPOT-PED INJECTION at room temperature between 68○F to 77○F (20○C to 25○C).
- Keep LUPRON DEPOT-PED INJECTION and all medicines out of the reach of children.

General information about the safe and effective use of LUPRON DEPOT-PED.
Medicines are sometimes prescribed for purposes other than those listed in a Medication Guide. Do not use LUPRON DEPOT-PED for a condition for which it was not prescribed.
This Medication Guide summarizes the most important information about LUPRON DEPOT-PED. If you would like more information, talk with your doctor. You can ask your pharmacist or doctor for information about LUPRON DEPOT-PED that is written for doctors or trained nurses.

What are the ingredients in LUPRON DEPOT-PED?
LUPRON DEPOT-PED 7.5 mg, 11.25 mg or 15 mg for 1-month administration:
Active Ingredients: leuprolide acetate for depot suspension
Inactive Ingredients: purified gelatin, DL-lactic and glycolic acids copolymer, D-mannitol, carboxymethylcellulose sodium, polysorbate 80, water for injection, USP, and glacial acetic acid, USP to control pH.
LUPRON DEPOT-PED 11.25 mg or 30 mg for 3-month administration:
Active Ingredients: leuprolide acetate for depot suspension
Inactive Ingredients: polylactic acid, D-mannitol, carboxymethylcellulose sodium, polysorbate 80, water for injection, USP, and glacial acetic acid, USP to control pH.
LUPRON DEPOT-PED 45 mg for 6-month administration:
Active Ingredients: leuprolide acetate for depot suspension
Inactive Ingredients: polylactic acid, D-mannitol, and stearic acid, carboxymethylcellulose sodium, D-mannitol, polysorbate 80, water for injection, USP, and glacial acetic acid, USP to control pH.
Manufactured for:
AbbVie Inc.
North Chicago, IL 60064
By Takeda Pharmaceutical Company Limited
Osaka, Japan 540-8645
LUPRON DEPOT PED and its design are trademarks of AbbVie Endocrine Inc.
© 2025 AbbVie. All rights reserved.
For more information, go to www.lupronped.com or call 1-800-633-9110.

This Medication Guide has been approved by the U.S. Food and Drug Administration.

Revised: November 2025

20097738

NDC 0074-2108-03

PEDIATRIC USE ONLY 7.5 mg for 1-month administration

Single Dose Administration Kit with prefilled dual-chamber syringe.

LUPRON DEPOT-PED®

(Leuprolide Acetate for Depot Suspension)

Dispense the accompanying Medication Guide to each patient.

7.5 mg for 1-month administration

FOR INTRAMUSCULAR INJECTION

The front chamber contains: leuprolide acetate 7.5 mg۰purified gelatin 1.3 mg۰DL-lactic & glycolic acids copolymer 66.2 mg۰D-mannitol 13.2 mg

The second chamber contains: D-mannitol 50 mg۰ carboxymethylcellulose sodium 5 mg۰polysorbate 80 1 mg۰water for injection, USP and glacial acetic acid, USP to control pH

Rx only

PACKAGE LABEL

NDC 0074-2282-03

PEDIATRIC USE ONLY 11.25 mg for 1-month administration

Single Dose Administration Kit with prefilled dual-chamber syringe.

LUPRON DEPOT-PED®

(Leuprolide Acetate for Depot Suspension)

Dispense the accompanying Medication Guide to each patient.

11.25 mg for 1-month administration

FOR INTRAMUSCULAR INJECTION

The front chamber contains: leuprolide acetate 11.25 mg۰purified gelatin 1.95 mg۰DL-lactic & glycolic acids copolymer 99.3 mg۰D-mannitol 19.8 mg

The second chamber contains: D-mannitol 50 mg۰carboxymethylcellulose sodium 5 mg۰polysorbate 80 1 mg۰water for injection, USP, and glacial acetic acid, USP to control pH

Rx only

PACKAGE LABEL

NDC 0074-2440-03

PEDIATRIC USE ONLY 15 mg for 1-month administration

Single Dose Administration Kit with prefilled dual-chamber syringe.

LUPRON DEPOT-PED®

(Leuprolide Acetate for Depot Suspension)

Dispense the accompanying Medication Guide to each patient.

15 mg for 1-month administration

FOR INTRAMUSCULAR INJECTION

The front chamber contains: leuprolide acetate 15 mg۰purified gelatin 2.6 mg۰DL-lactic & glycolic acids copolymer 132.4 mg۰D-mannitol 26.4 mg

The second chamber contains: D-mannitol 50 mg۰ carboxymethylcellulose sodium 5 mg۰polysorbate 80 1 mg۰water for injection, USP and glacial acetic acid, USP to control pH

Rx only

PACKAGE LABEL

NDC 0074-3779-03

PEDIATRIC USE ONLY 11.25 mg for 3-month administration

Single Dose Administration Kit with prefilled dual-chamber syringe.

LUPRON DEPOT-PED® (Leuprolide Acetate for Depot Suspension)

Dispense the accompanying Medication Guide to each patient.

11.25 mg for 3-month administration

FOR INTRAMUSCULAR INJECTION

The front chamber contains: leuprolide acetate 11.25 mg۰polylactic acid 99.3 mg۰D-mannitol 19.45 mg

The second chamber contains: carboxymethylcellulose sodium 7.5 mg۰D-mannitol 75.0 mg۰polysorbate 80 1.5 mg۰water for injection, USP, and glacial acetic acid, USP to control pH

Rx only

PACKAGE LABEL

NDC 0074-9694-03

PEDIATRIC USE ONLY 30 mg for 3-month administration

Single Dose Administration Kit with prefilled dual-chamber syringe

LUPRON DEPOT-PED®

(Leuprolide Acetate for Depot Suspension)

Dispense the accompanying Medication Guide to each patient.

30 mg for 3-month administration

FOR INTRAMUSCULAR INJECTION

The front chamber contains: leuprolide acetate 30 mg۰polylactic acid 264.8 mg۰D-mannitol 51.9 mg

The second chamber contains: carboxymethylcellulose sodium 7.5 mg۰D-mannitol 75.0 mg۰polysorbate 80 1.5 mg۰water for injection, USP, and glacial acetic acid, USP to control pH

Rx only

PACKAGE LABEL

NDC 0074-3575-01

PEDIATRIC USE ONLY 45 mg for 6-month administration

Single Dose Administration Kit with prefilled dual-chamber syringe

LUPRON DEPOT-PED®

(Leuprolide Acetate for Depot Suspension)

Dispense the accompanying Medication Guide to each patient.

45 mg for 6-month administration

FOR INTRAMUSCULAR INJECTION

The front chamber contains: leuprolide acetate 45 mg۰polylactic acid 169.9 mg۰D-mannitol 39.7 mg۰stearic acid 10.1 mg

The second chamber contains: carboxymethylcellulose sodium 7.5 mg۰D-mannitol 75.0 mg۰polysorbate 80 1.5 mg۰water for injection, USP, and glacial acetic acid, USP to control pH

Rx only